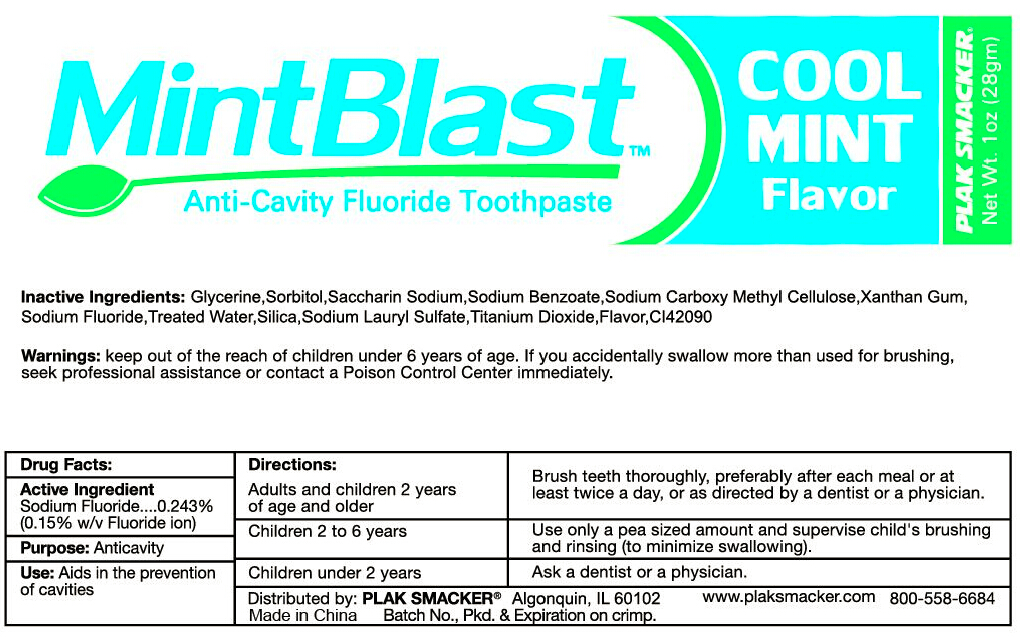 DRUG LABEL: MintBlast Anti Cavity Fluoride
NDC: 71035-300 | Form: PASTE
Manufacturer: Yangzhou Hongshengding Chemical Co.,Ltd.
Category: otc | Type: HUMAN OTC DRUG LABEL
Date: 20180106

ACTIVE INGREDIENTS: SODIUM FLUORIDE 0.243 g/100 g
INACTIVE INGREDIENTS: DISODIUM CARBOXYMETHYLARSONATE; SORBITOL; GLYCERIN; XANTHAN GUM; SACCHARIN SODIUM; SODIUM BENZOATE; WATER; SODIUM SILICATE; SODIUM LAURYL SULFATE; TITANIUM DIOXIDE

Anti Cavity Fluoride Toothpaste

Active ingredients

Sodium Fluoride 0.243%(0.15% w/v Fluoride ion)

Purpose

anticavity

Uses

Aids in the prevention of cavities.

Warnings

Keep out of the reach of children under 6 years of age.if you accidentally swallow more than used for brushing.seek professional assisatance or contact a Poison Control Center immediately.

Keep out of reach of children.

Directions

Adults and children 2years of age and older:Brush teeth thoroughly,preferably after each meal or at least twice a day,or as directed by a dentist or a physician.

Children 2-6 years:Use only a pea sized amount and supervise child's brushing and rinsing (to minimize swallowing)

Children under 2 years:Ask a dentist or a physician.

INACTIVE INGREDIENT

Glycerine,Sorbitol,Saccharin Sodium,Sodium benzoate,Sodium Carboxy Methyl Cellulose,Xanthan Gum,Sodium Fluoride,Treated Water,Silica,Sodium Lauryl Sulfate,Tianium Dioxide,Flavor,CI42090